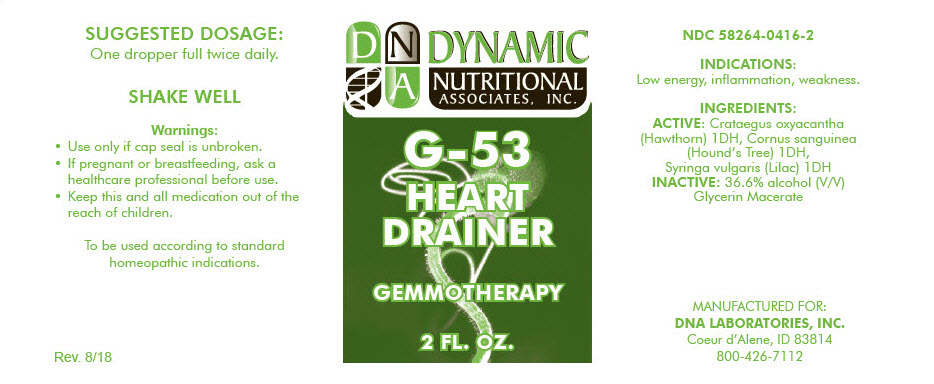 DRUG LABEL: G-53
NDC: 58264-0416 | Form: SOLUTION
Manufacturer: DNA Labs, Inc.
Category: homeopathic | Type: HUMAN OTC DRUG LABEL
Date: 20250109

ACTIVE INGREDIENTS: HAWTHORN LEAF WITH FLOWER 1 [hp_X]/1 mL; CORNUS SANGUINEA WHOLE 1 [hp_X]/1 mL; SYRINGA VULGARIS FLOWER 1 [hp_X]/1 mL
INACTIVE INGREDIENTS: ALCOHOL; WATER

G-53

NDC 58264-0416-2

INDICATIONS

PURPOSE

Low energy, inflammation, weakness.

INGREDIENTS

ACTIVE

Crataegus oxyacantha (Hawthorn) 1DH, Cornus sanguinea (Hound's Tree) 1DH, Syringa vulgaris (Lilac) 1DH

INACTIVE

36.6% alcohol (V/V) Glycerin Macerate

SUGGESTED DOSAGE

One dropper full twice daily.

STORAGE AND HANDLING

SHAKE WELL

Warnings

- Use only if cap seal is unbroken.

PREGNANCY OR BREAST FEEDING

- If pregnant or breastfeeding, ask a healthcare professional before use.

KEEP OUT OF REACH OF CHILDREN

- Keep this and all medication out of the reach of children.

To be used according to standard homeopathic indications.

PRINCIPAL DISPLAY PANEL - 2 FL. OZ. Bottle Label

DYNAMIC
NUTRITIONAL
ASSOCIATES, INC.

G-53

HEART
DRAINER

GEMMOTHERAPY

2 FL. OZ.